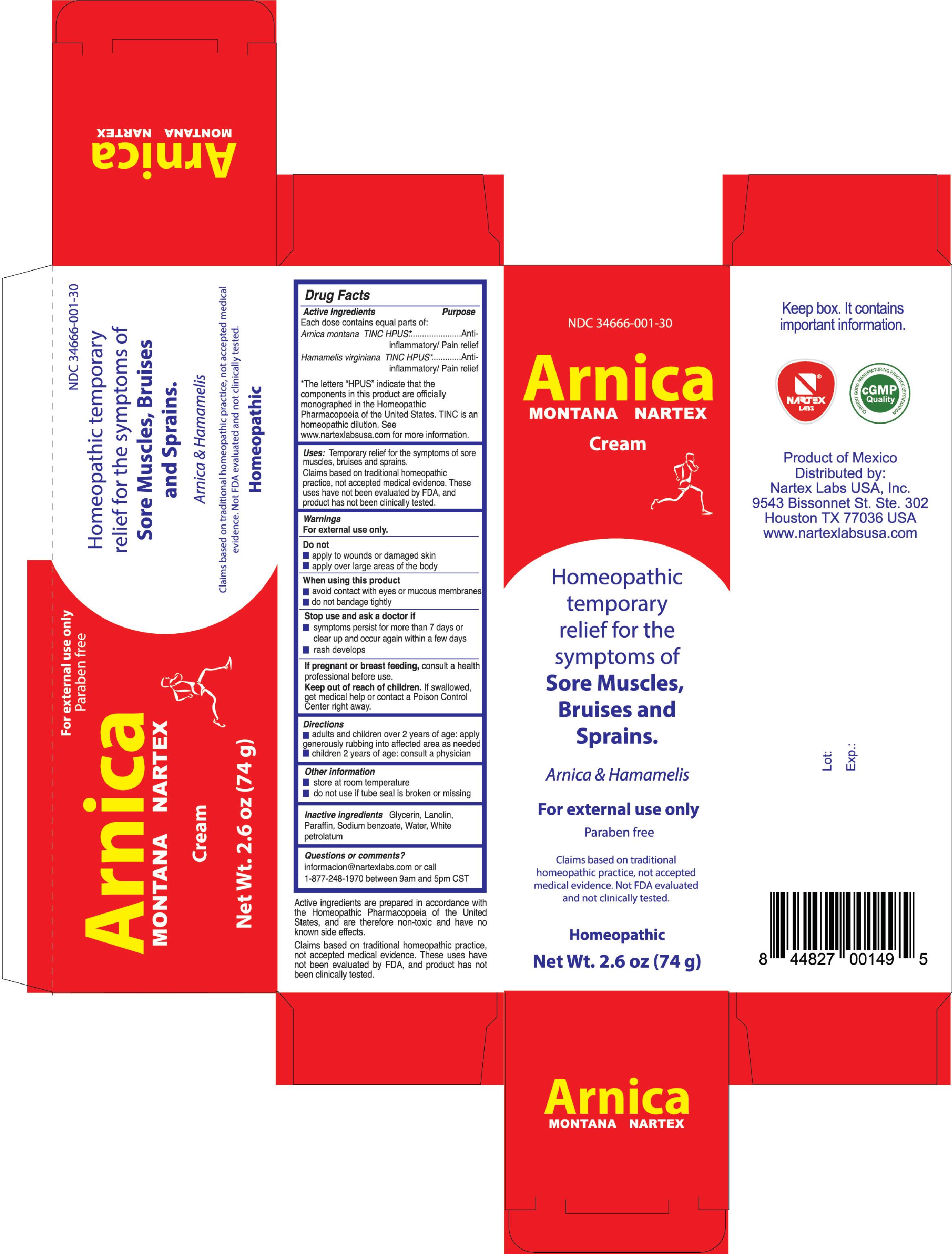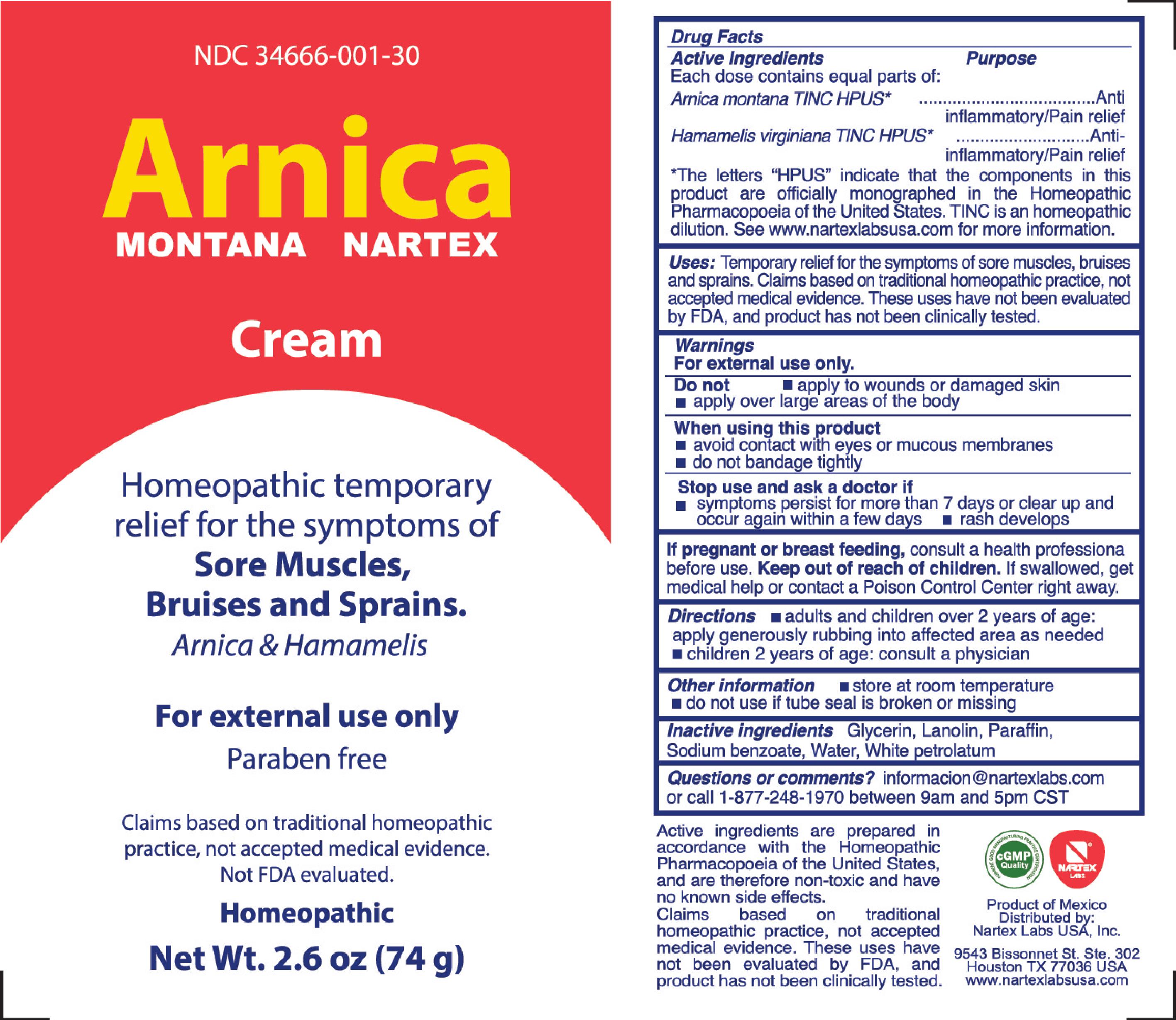 DRUG LABEL: Arnica Montana Nartex
NDC: 34666-001 | Form: CREAM
Manufacturer: NARTEX LABORATORIOS HOMEOPATICOS SA DE CV
Category: homeopathic | Type: HUMAN OTC DRUG LABEL
Date: 20220123

ACTIVE INGREDIENTS: ARNICA MONTANA 1.73 g/29.7 g; HAMAMELIS VIRGINIANA LEAF 0.0178 g/29.7 g
INACTIVE INGREDIENTS: PETROLATUM; LANOLIN; GLYCERIN; PARAFFIN; SODIUM BENZOATE; WATER

Active Ingredients

Each dose contains equal parts of:

Arnica montana TINC HPUS

Hamamelis virginiana TINC HPUS

The letters "HPUS" indicate that the components in this product are officially monographed in the Homeopathic Pharmacopoeia of the United States. TINC is an homeopathic dilution. See www.nartexlabsusa.com for more information.

Purpose

Each dose contains equal parts of:

Arnica montana TINC HPUS*............Anti-inflammatory/Pain Relief

Hamamelis virginiana TINC HPUS*..........Anti-inflammatory/Pain Relief

The letters "HPUS" indicate that the components in this product are officially monographed in the Homeopathic Pharmacopoeia of the United States. TINC is an homeopathic dilution. See www.nartexlabsusa.com for more information.

Uses

Temporary relief for the symptoms of sore muscles, bruises and sprains.

Claims based on traditional homeopathic practice, not accepted medical evidence. These uses have not been evaluated by FDA, and product has not been clinically tested.

Warnings

For external use only.

Do not

- apply to wounds or damaged skin
- apply over large areas of the body

When using this product

- avoid contact with eyes or mucous membranes
- do not bandage tightly

Stop use and ask a doctor if

- symptoms persist for more than 7 days or clear up and occur again within a few days
- rash develops

PREGNANCY OR BREAST FEEDING

If pregnant or breast feeding, consult a health professional before use.

Keep out of reach of children. If swallowed, get medical help or contact a Poison Control Center right away.

Directions

- adults and children over 2 years of age: apply generously rubbing into affected area as needed
- children 2 years of age: consult a physician

Other information

- store at room temperature
- do not use if tube seal is broken or missing

Inactive ingredients

Glycerin, Lanolin, Paraffin, Sodium benzoate, Water, White petrolatum

Questions or comments?

informacion@nartexlabs.com or call 1-877-248-1970 between 9am and 5pm CST

Principal Display Panel

NDC 34666-001-30

Arnica Montana Nartex Cream

Homeopathic temporary relief for the symptoms of Sore Muscles, Bruises and Sprains.

Arnica & Hamamelis

For external use only

Paraben free

Claims based on traditional homeopathic practice, not accepted medical evidence. Not FDA evaluated and not clinically tested.

Homeopathic

Net Wt. 2.6oz (74 g)